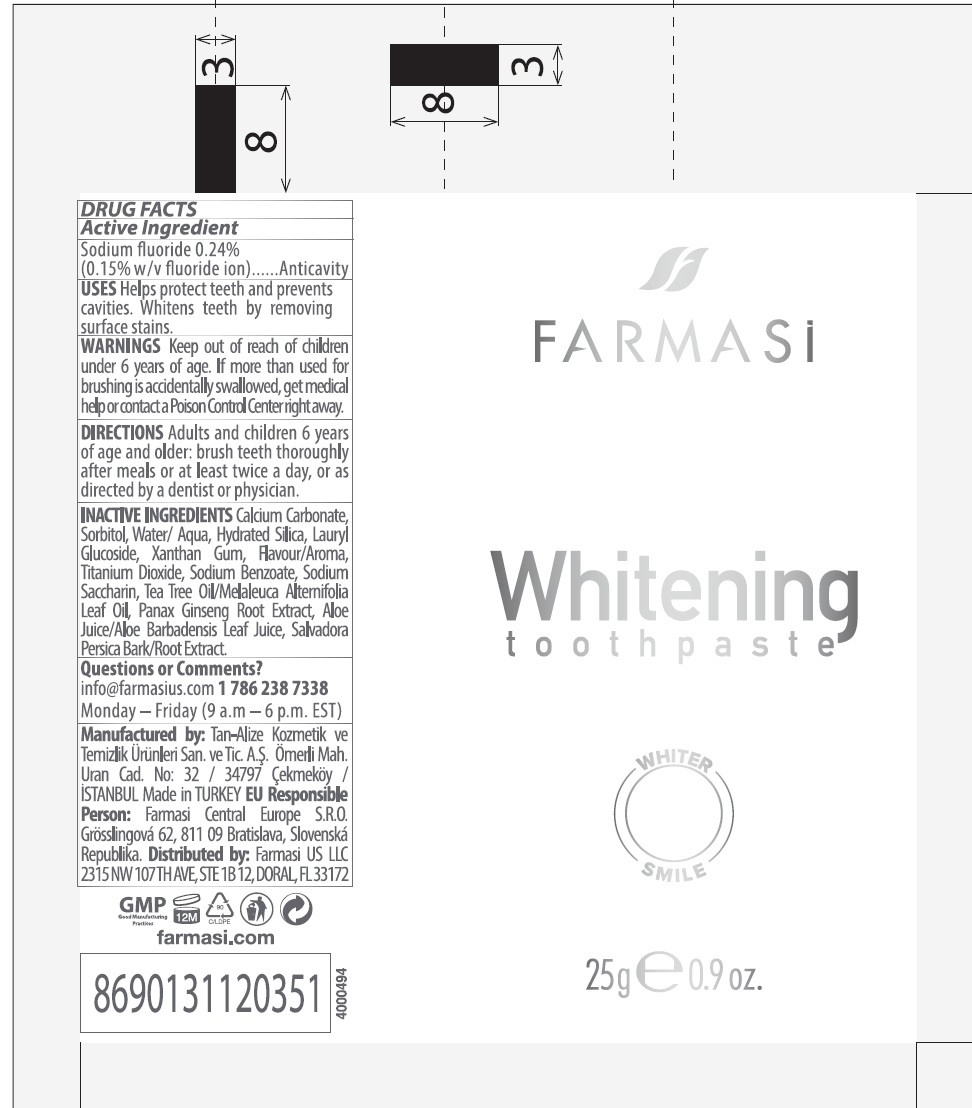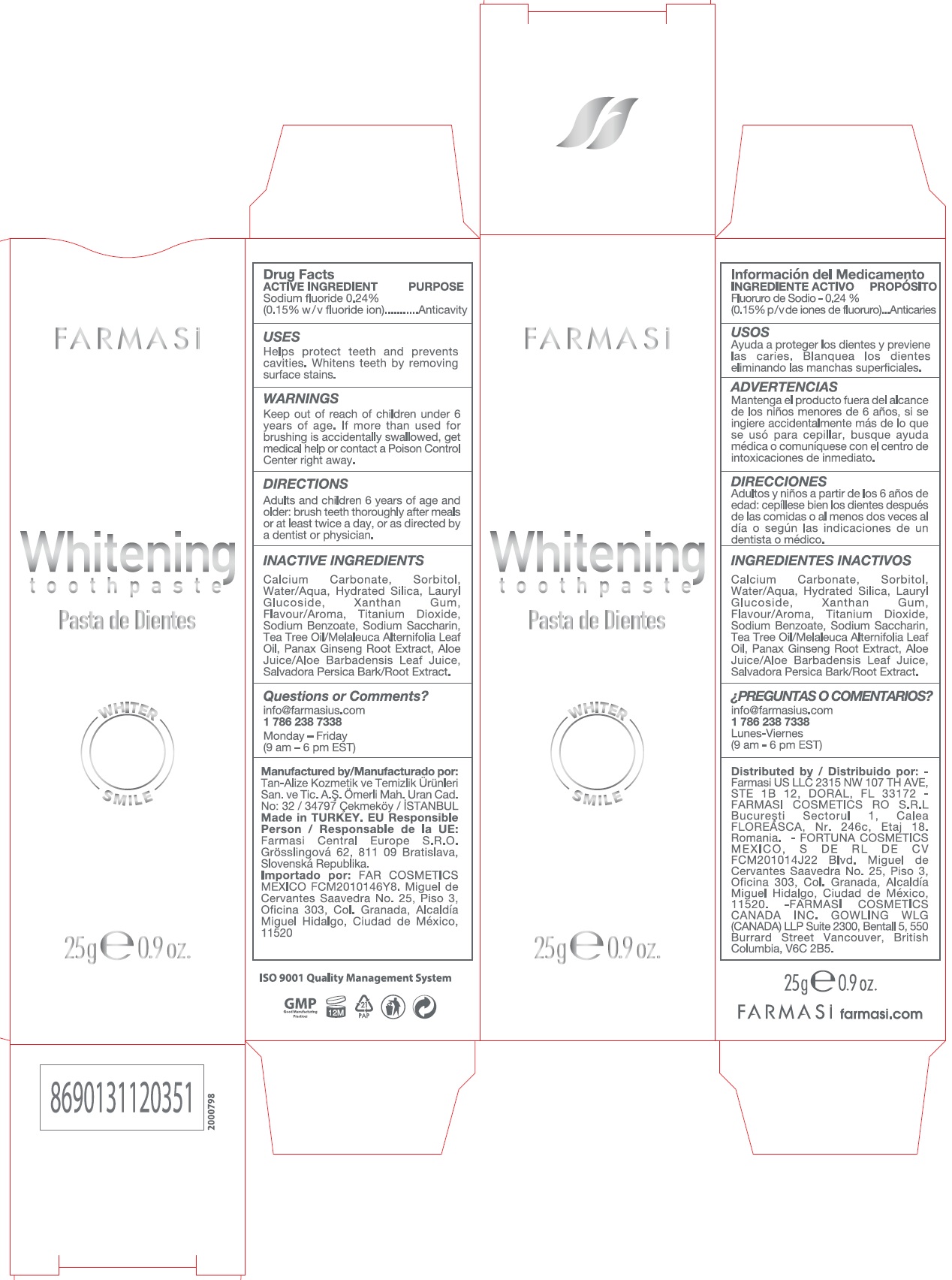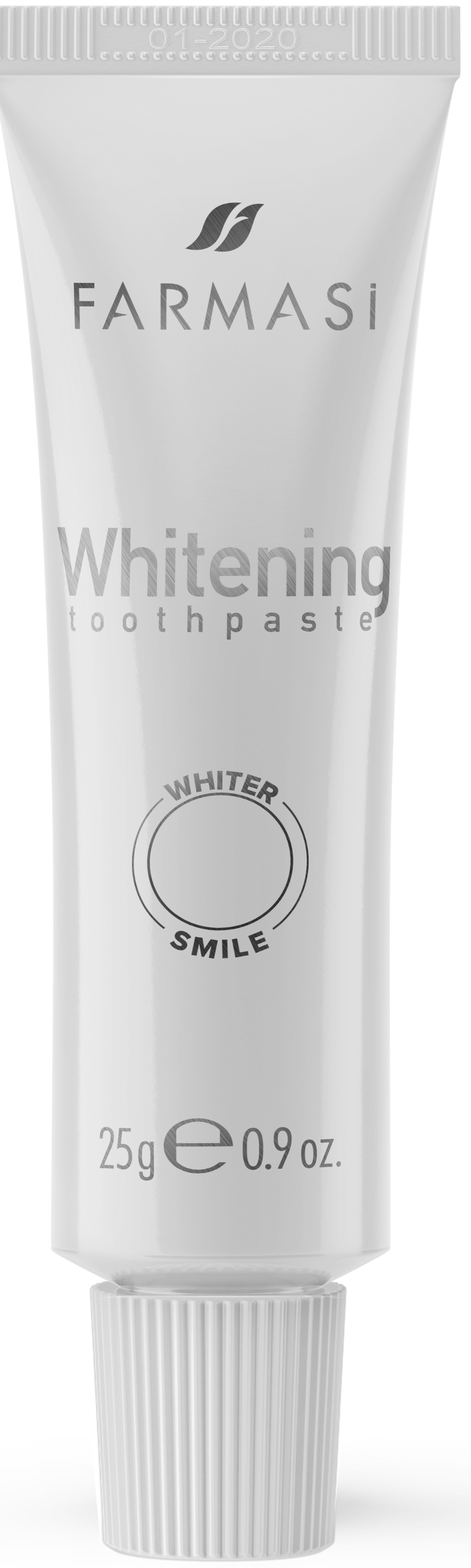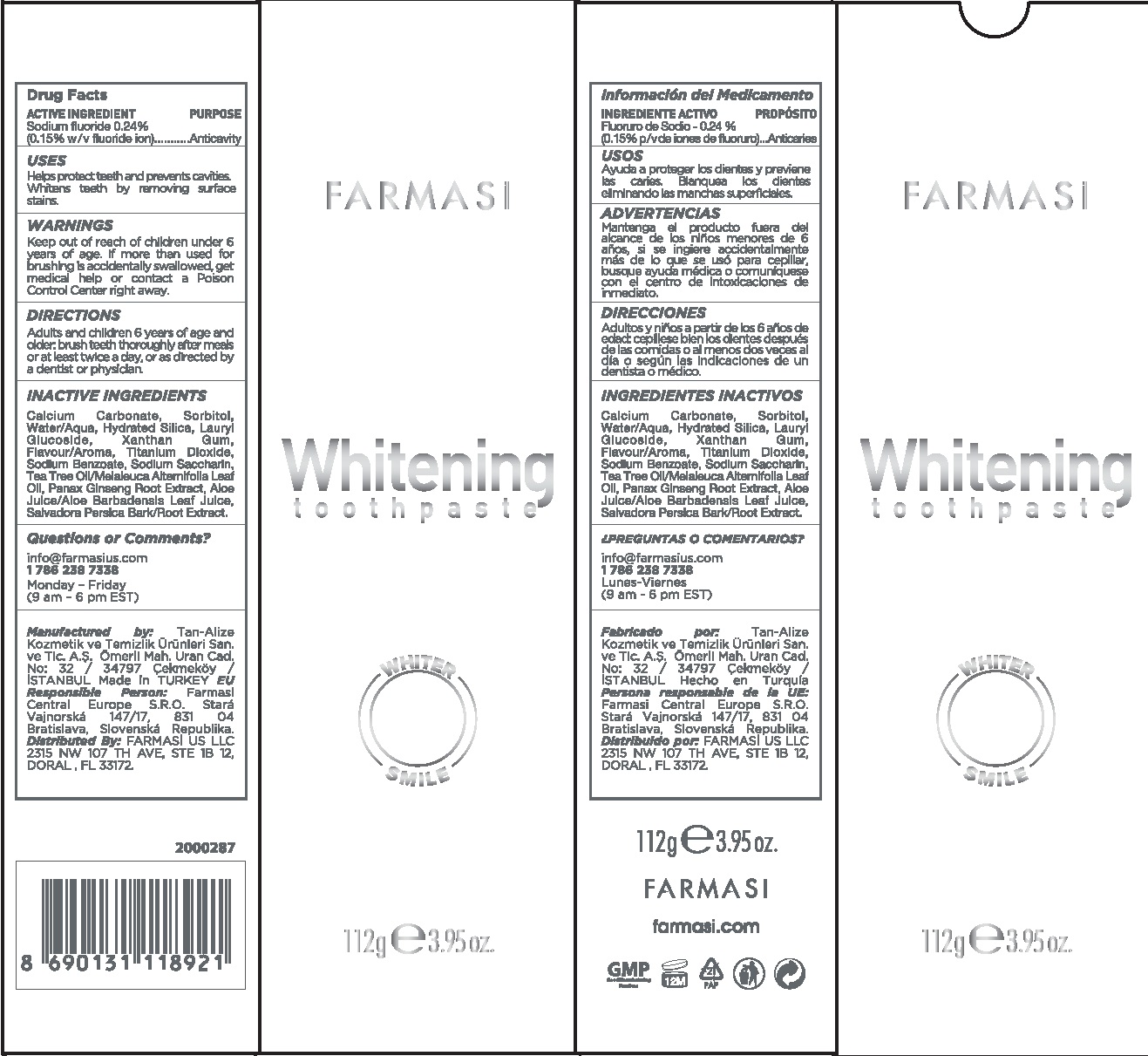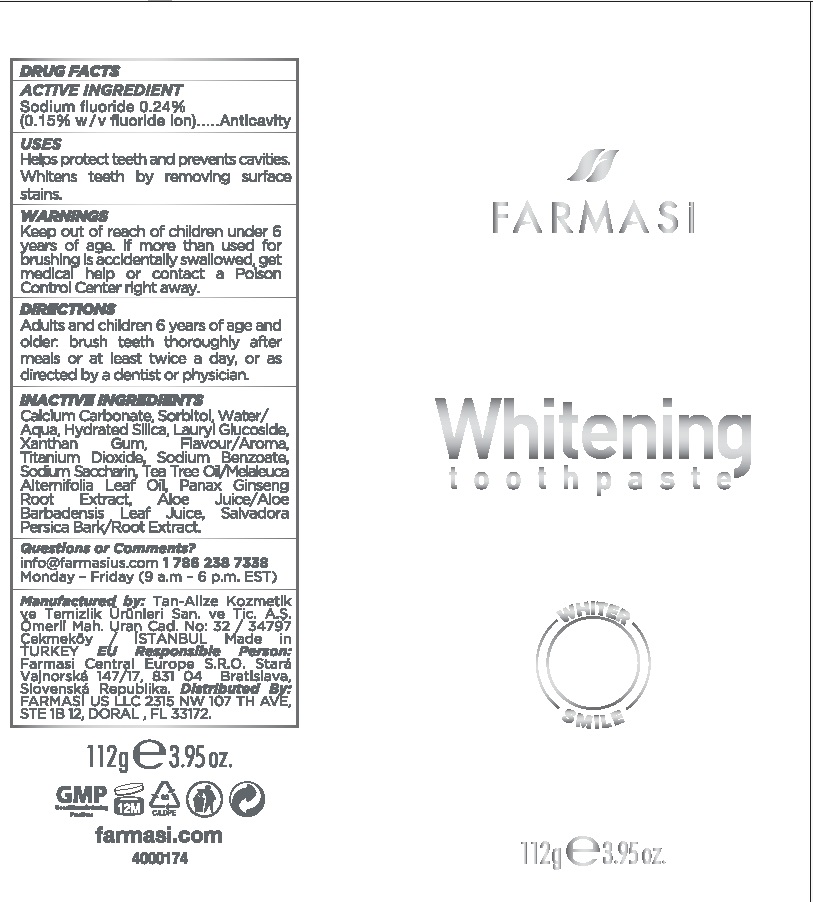 DRUG LABEL: Farmasi Whitening
NDC: 74690-012 | Form: PASTE, DENTIFRICE
Manufacturer: Farmasi US LLC
Category: otc | Type: HUMAN OTC DRUG LABEL
Date: 20231105

ACTIVE INGREDIENTS: SODIUM FLUORIDE 1.5 mg/1 g
INACTIVE INGREDIENTS: CALCIUM CARBONATE; SORBITOL; WATER; HYDRATED SILICA; LAURYL GLUCOSIDE; XANTHAN GUM; TITANIUM DIOXIDE; SODIUM BENZOATE; SACCHARIN SODIUM; TEA TREE OIL; ASIAN GINSENG; ALOE VERA LEAF; SALVADORA PERSICA ROOT

Farmasi Whitening Toothpaste

ACTIVE INGREDIENTS

Sodium Fluoride 0.24 % (0.15% w/v fluoride ion)

PURPOSE

Anticavity

USES

Helps proctect teeth and prevents cavities. Whitens teeth by removing surface stains.

WARNINGS

Keep out of reach of children

under 6 years of age. If more than used for brushing in accidentally swallowed, get medical help or contact a Poison Control Center right away.

DIRECTIONS

Adults and children 6 years of age and older: brush teeth thoroughly after meals of at least twice a day, or as directed by a dentist or physician.

INACTIVE INGREDIENTS

Calcium Carbonate, Sorbitol, Water/Aqua, Hydrated Silica, Lauryl Glucoside, Xanthan Gum, Flavour/Aroma, Titanium Dioxide, Sodium Benzoate, Sodium Saccharin, Tea Tree Oil/Melaleuca Alternifolia Leaf Oil, Panax Ginseng Root Extract, Aloe Juice/Aloe Barbadensis Leaf Juice, Salvadora Persica Bark/Root Extract.

Questions or Comments?

info@farmasius.com Monday - Friday (9 a.m - 6 p.m.EST) 1 786 238 7338